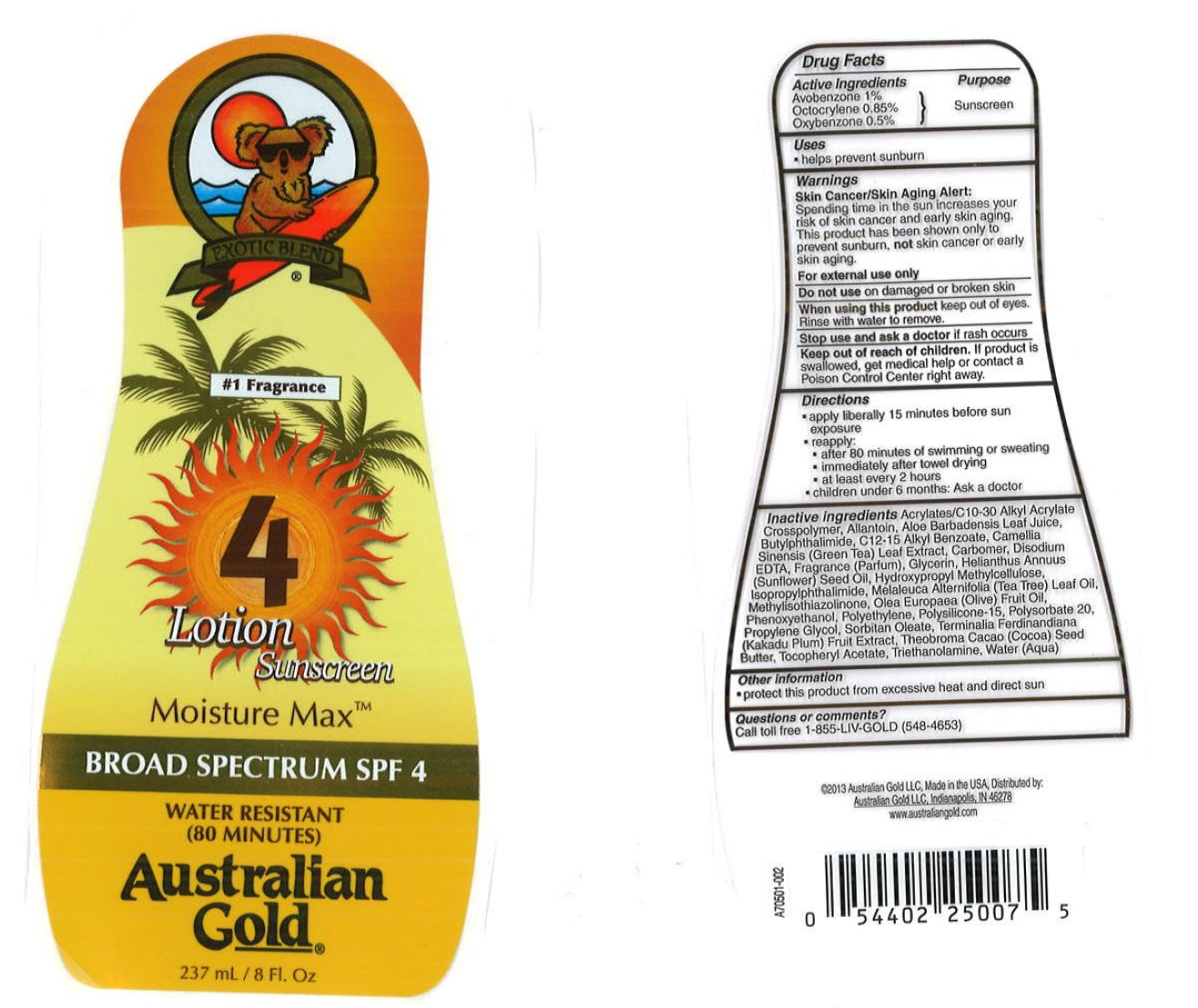 DRUG LABEL: Australian Gold
NDC: 58443-0220 | Form: LOTION
Manufacturer: Prime Enterprises Inc.
Category: otc | Type: HUMAN OTC DRUG LABEL
Date: 20200117

ACTIVE INGREDIENTS: AVOBENZONE 9.74 mg/1 mL; OCTOCRYLENE 8.28 mg/1 mL; OXYBENZONE 4.87 mg/1 mL
INACTIVE INGREDIENTS: TEA TREE OIL; COCOA BUTTER; EDETATE DISODIUM; GLYCERIN; HYPROMELLOSES; OLIVE OIL; HIGH DENSITY POLYETHYLENE; POLYSORBATE 20; PROPYLENE GLYCOL; SORBITAN MONOOLEATE; CARBOMER 940; GREEN TEA LEAF; ALKYL (C12-15) BENZOATE; SUNFLOWER OIL; ALOE VERA LEAF; (C10-C30)ALKYL METHACRYLATE ESTER; KAKADU PLUM; ALPHA-TOCOPHEROL ACETATE; ALLANTOIN; WATER; PHENOXYETHANOL; N-BUTYLPHTHALIMIDE; TROLAMINE; POLYSILICONE-15; METHYLISOTHIAZOLINONE; ISOPROPYLPHTHALIMIDE

Australian Gold Broad Spectrum SPF 4 Sunscreen

Active Ingredients

Avobenzone 1%

Octocrylene 0.85%

Oxybenzone 0.5%

Purpose

Sunscreen

Uses

- helps prevent sunburn

WARNINGS

Skin Cancer/ Skin Aging Alert:

Spending time in the sun increases your risk of skin cancer and early skin aging. This product has been shown only to prevent sunburn, not skin cancer or early skin aging.

For external use only

Do not use on damaged or broken skin

When using this product keep out of eyes. Rinse with water to remove.

Stop use and ask a doctor if rash occurs

Keep out of reach of children. If product is swallowed, get medical help or contact a Poison Control Center right away.

Directions

- apply liberally 15 minutes before sun exposure
- reapply:
- after 80 minutes of swimming or sweating
- immediately after towel drying
- at least every 2 hours
- children under 6 months: Ask a doctor

INACTIVE INGREDIENT

Acrylates/C10-30 Alkyl Acrylate Crosspolymer, Allantoin, Aloe Barbadensis Leaf Juice, Butylphthalimide, C12-15 Alkyl Benzoate, Camellia Sinensis (Green Tea) Leaf Extract, Carbomer, Disodium EDTA, Fragrance (Parfum), Glycerin, Helianthus Annuus (Sunflower) Seed Oil, Hydroxypropyl Methylcellulose, Isopropylphthalimide, Melaleuca Alternifolia (Tea Tree) Leaf Oil, Methylisothiazolinone, Olea Europaea (Olive) Fruit Oil, Phenoxyethanol, Polyethylene, Polysilicone-15, Polysorbate 20, Propylene Glycol, Sorbitan Oleate, Terminalia Ferdinandiana (Kakadu Plum) Fruit Extract, Theobroma Cacao (Cocoa) Seed Butter, Tocopheryl Acetate, Triethanolamine, Water (Aqua)

Other Information

- protect this product from excesive heat and direct sun

Questions or Comments?

Call toll free 1-855-LIV-GOLD (548-4653)